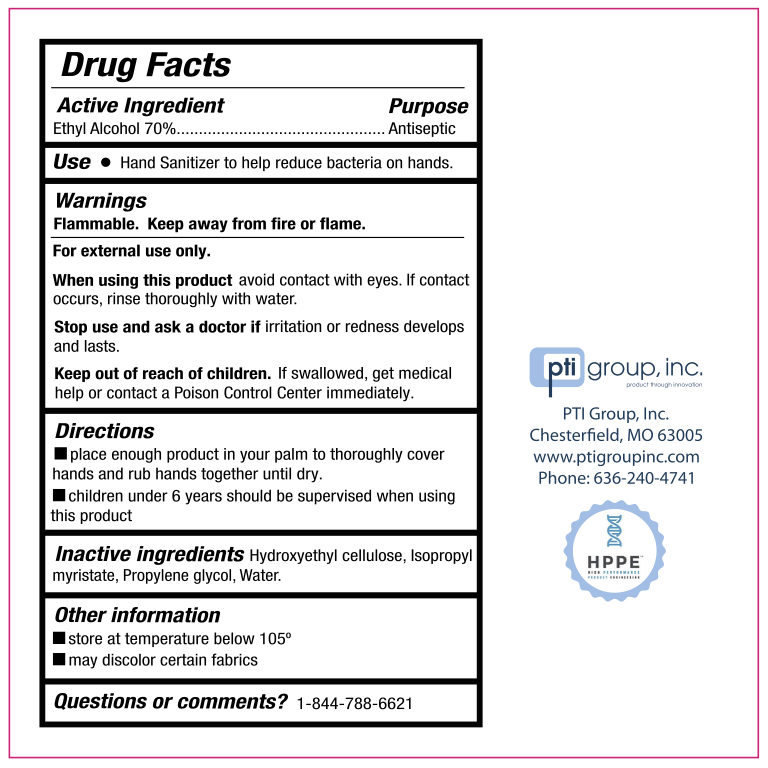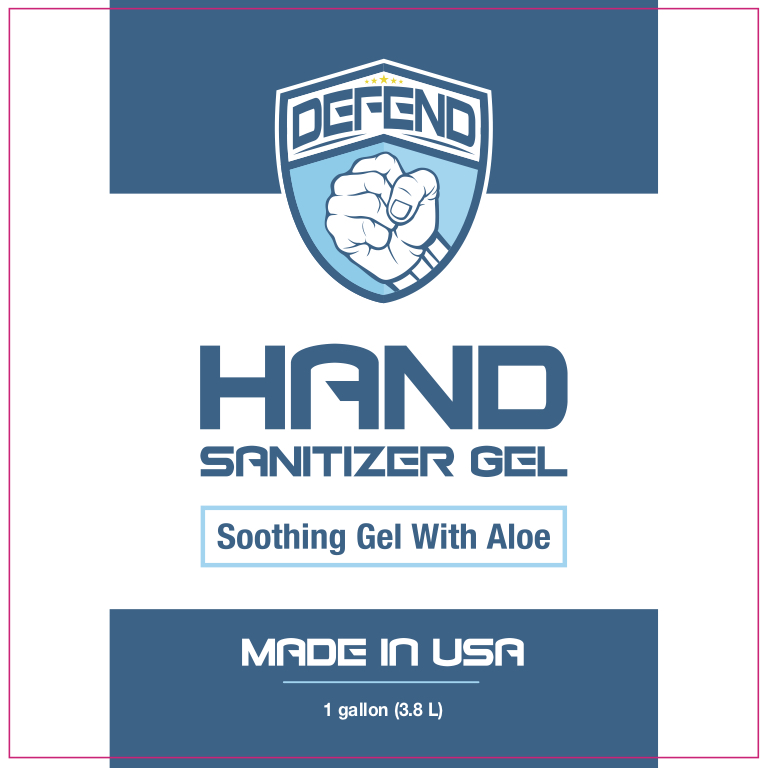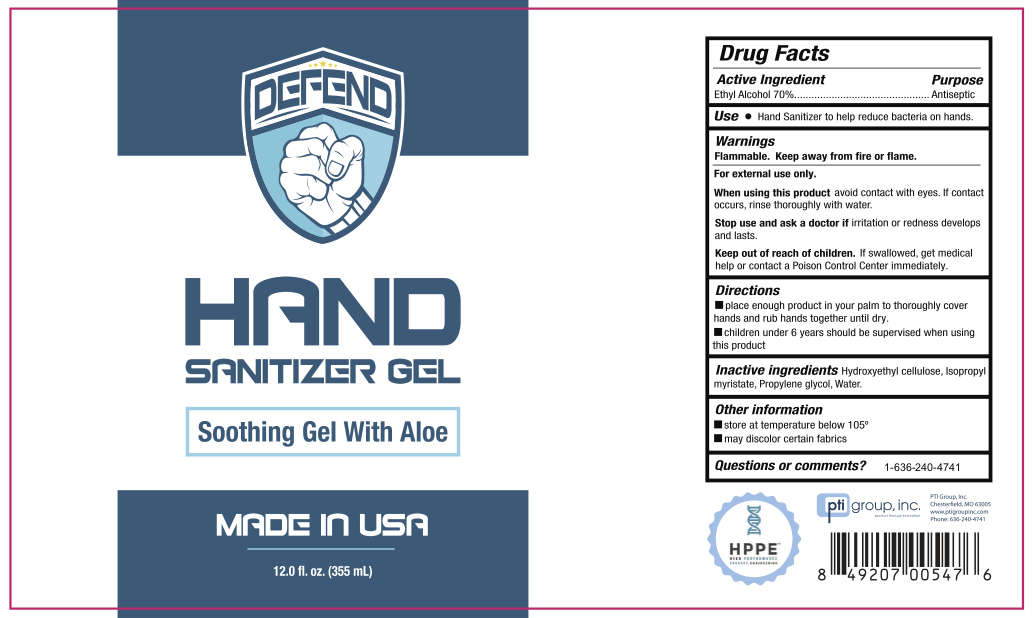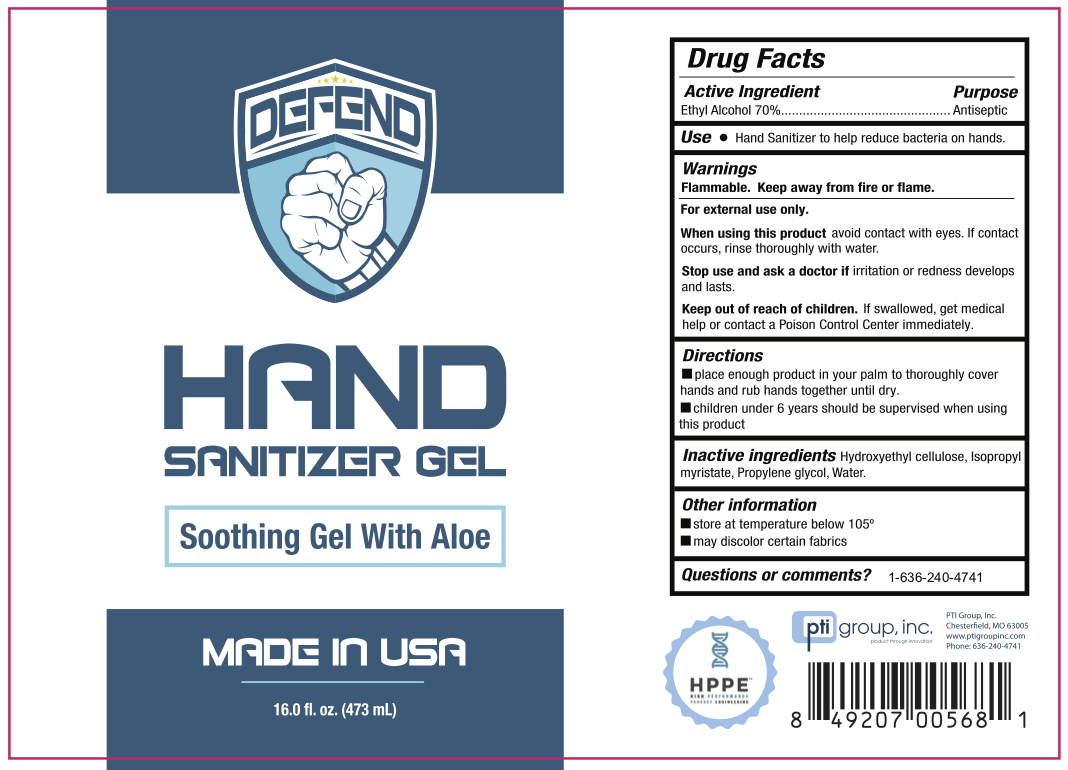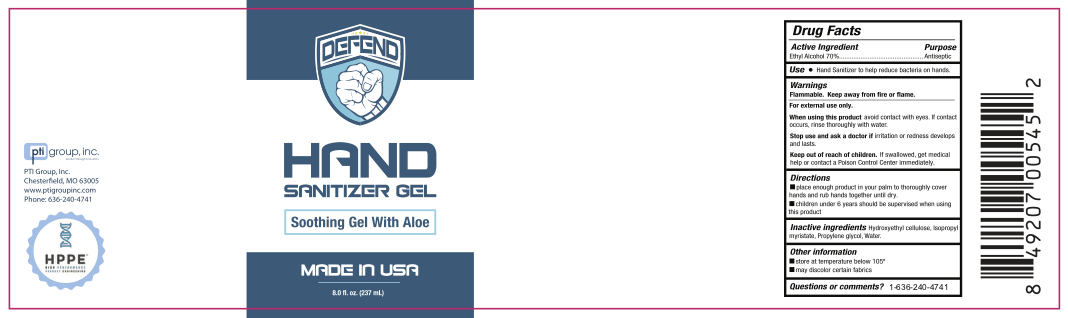 DRUG LABEL: Hand Sanitizer
NDC: 58039-119 | Form: GEL
Manufacturer: HPPE, LLC
Category: otc | Type: HUMAN OTC DRUG LABEL
Date: 20200617

ACTIVE INGREDIENTS: ALCOHOL 70 mL/100 mL
INACTIVE INGREDIENTS: PROPYLENE GLYCOL; WATER; ISOPROPYL MYRISTATE; HYDROXYETHYL CELLULOSE, UNSPECIFIED

ACTIVE INGREDIENT

Alcohol 70% v/v. Purpose: Antiseptic

PURPOSE

Antiseptic, Hand Sanitizer

USE

Hand Sanitizer to help reduce bacteria that potentially can cause disease. For use when soap and water are not available.

WARNINGS

For external use only. Flammable. Keep away from heat or flame.

DO NOT USE

- in children less than 2 months of age
- on open skin wounds

When using this product keep out of eyes, ears, and mouth. In case of contact with eyes, rinse eyes thoroughly with water.

Stop use and ask a doctor if irritation or rash occurs. These may be signs of a serious condition.

Keep out of reach of children. If swallowed, get medical help or contact a Poison Control Center right away.

Stop use and ask a doctor if irritation or rash occurs. These may be signs of a serious condition.

Keep out of reach of children. If swallowed, get medical help or contact a Poison Control Center right away.

DIRECTIONS

- Place enough product on hands to cover all surfaces. Rub hands together until dry.
- Supervise children under 6 years of age when using this product to avoid swallowing.

OTHER INFORMATION

- Store between 15-30C (59-86F).
- Avoid freezing and excessive heat above 40C (104F).

INACTIVE INGREDIENTS

hydroxyethylcellulose, isopropyl myristate, propylene glycol, water

PACKAGE LABEL - PRINCIPAL DISPLAY PANEL

237 mL NDC: 58039-119-03

355 mL NDC: 58039-119-04

473 mL NDC: 58039-119-05

3.8 L NDC: 58039-119-06